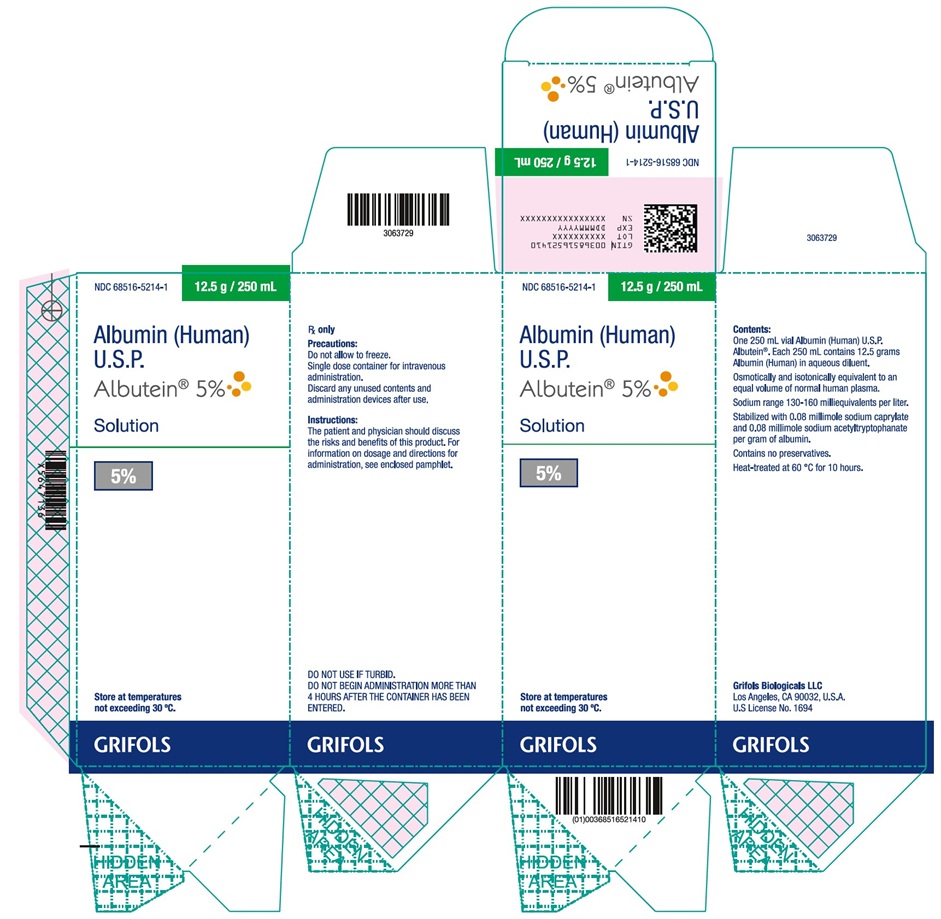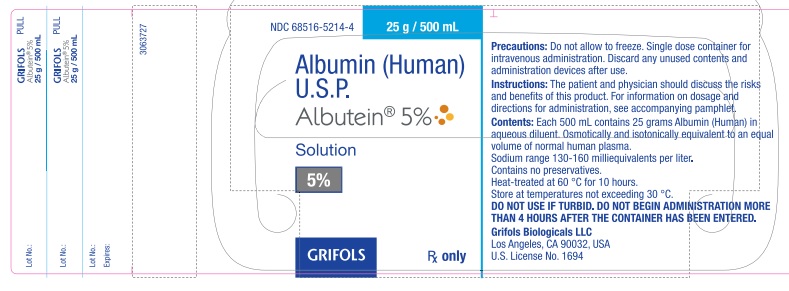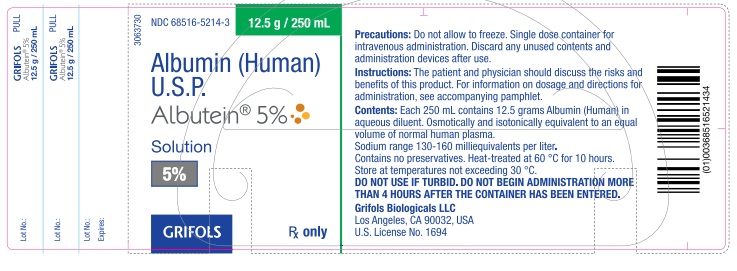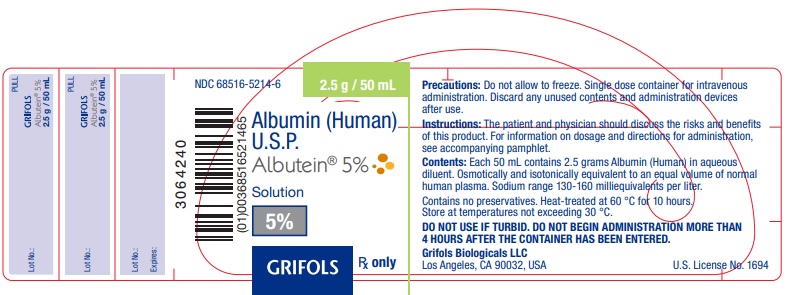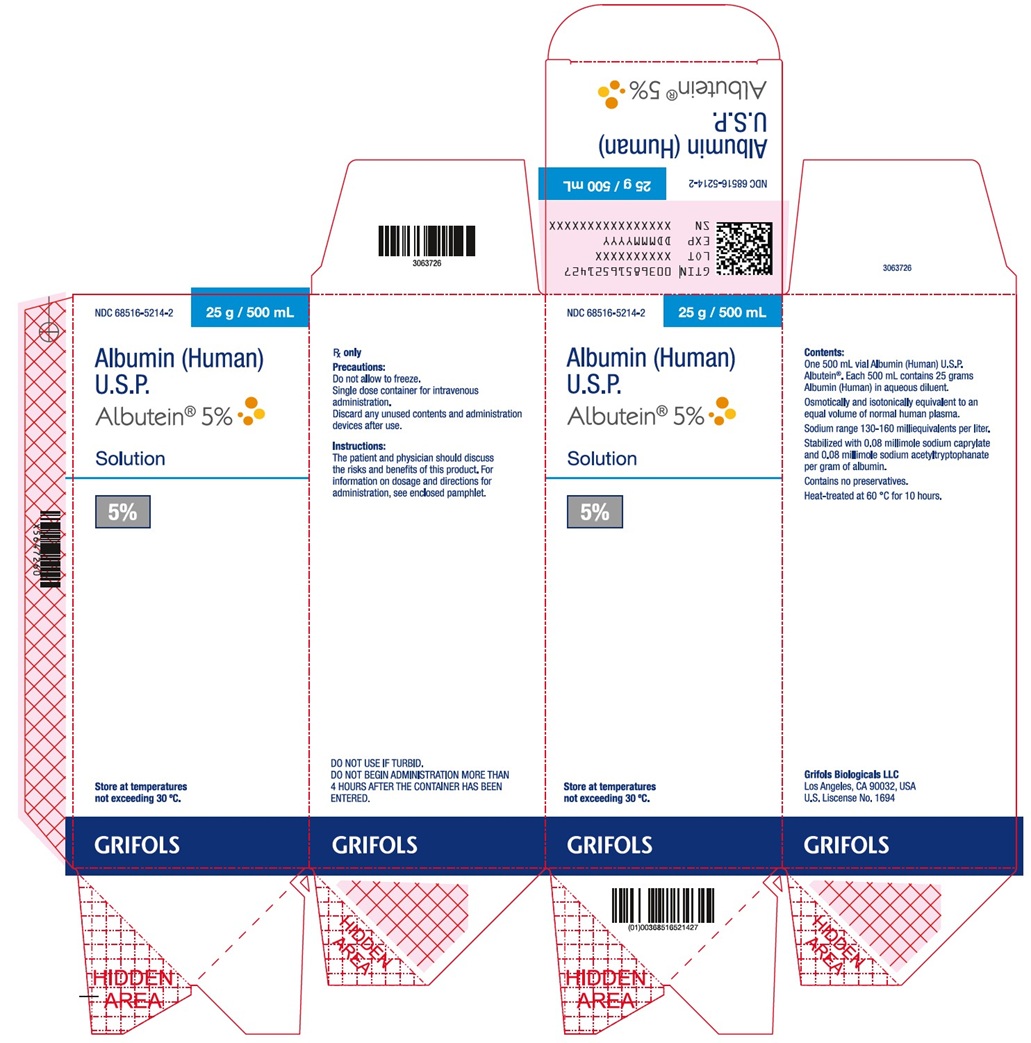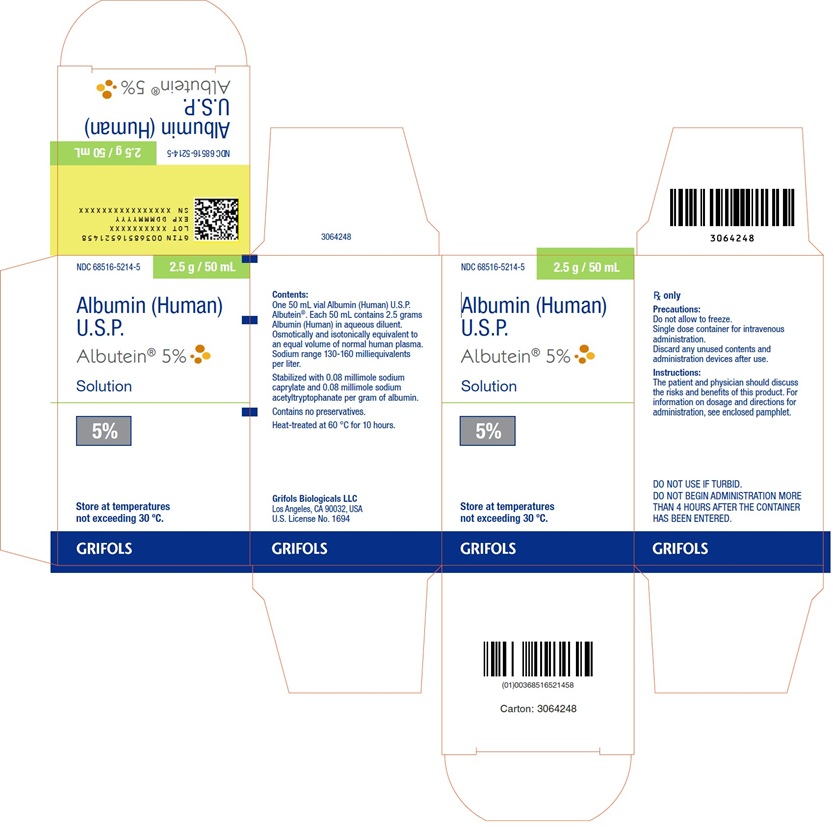 DRUG LABEL: ALBUTEIN
NDC: 68516-5214 | Form: INJECTION, SOLUTION
Manufacturer: GRIFOLS USA, LLC
Category: other | Type: PLASMA DERIVATIVE
Date: 20250528

ACTIVE INGREDIENTS: Albumin Human 12.5 g/250 mL
INACTIVE INGREDIENTS: Sodium Chloride; Sodium Caprylate; Sodium Acetyltryptophanate; Water

HIGHLIGHTS OF PRESCRIBING INFORMATION

These highlights do not include all the information needed to use ALBUTEIN 5% safely and effectively. See full prescribing information for ALBUTEIN 5%.
ALBUTEIN 5% (albumin [human] U.S.P.)
5% solution
Initial U.S. Approval: 1978

1 INDICATIONS AND USAGE

ALBUTEIN 5% is an albumin solution indicated for:

- Hypovolemia. (1.1)
- Cardiopulmonary bypass procedures. (1.2)
- Hypoalbuminemia. (1.3)
- Plasma exchange. (1.4)

2 DOSAGE AND ADMINISTRATION

For Intravenous Use Only

Dosage and infusion rate should be adjusted to the patient's individual requirements.

Indication | Dose
Hypovolemia | Adults: Initial dose of 20 g (including renal dialysis). For acute liver failure: initial dose of 12 to 25 g. (2.1)
Cardiopulmonary bypass procedures | Adults: Initial dose of 25 g. (2.1)
Hypoalbuminemia | Adults: 50 to 75 g For pre- and post-operative hypoproteinemia: 50 to 75 g. For burn therapy after the first 24 h: initial dose of 25 g and dose adjustment to maintain plasma protein concentration of 2.5 g per 100 mL. Third space protein loss due to infection: initial dose of 50 to 100 g. (2.1)
Plasma exchange | The dose required depends on the volume of plasma removed during the procedure.

Do not dilute with sterile water for injection as this may cause hemolysis in recipients. (5.6)

3 DOSAGE FORMS AND STRENGTHS

ALBUTEIN 5% is a solution containing 50 g per L of total protein of which at least 95% is human albumin.

4 CONTRAINDICATIONS

- Hypersensitivity to albumin preparations or to any of the excipients.
- Severe anemia or cardiac failure with normal or increased intravascular volume. (4)

5 WARNINGS AND PRECAUTIONS

- Suspicion of allergic or anaphylactic reactions requires immediate discontinuation of the injection and implementation of appropriate medical treatment. (5.1)
- Hypervolemia may occur if the dosage and rate of infusion are not adjusted to the patient's volume status. Use with caution in conditions where hypervolemia and its consequences or hemodilution could represent a special risk to the patient. (5.2)
- Monitor electrolytes, coagulation and hematology parameters, and hemodynamic status when albumin is given. (5.3, 5.4, 5.5)
- Do not dilute with sterile water for injection. (5.6)
- Albumin is a derivative of human blood. Based on effective donor screening and product manufacturing processes, it carries an extremely remote risk of transmission of viral diseases and variant Creutzfeldt-Jakob disease (vCJD). There is a theoretical risk for transmission of Creutzfeldt-Jakob disease (CJD), but if that risk actually exists, the risk of transmission would also be considered extremely remote. No cases of transmission of viral diseases, CJD or vCJD have ever been identified for ALBUTEIN 5%. (5.7)

6 ADVERSE REACTIONS

The most common adverse reactions are anaphylactoid type reactions. (6)

To report SUSPECTED ADVERSE REACTIONS, contact Grifols Biologicals LLC at 1-888-GRIFOLS (1-888-474-3657) or FDA at 1-800-FDA-1088 or www.fda.gov/medwatch.

FULL PRESCRIBING INFORMATION

1 INDICATIONS AND USAGE

1.1 Hypovolemia

For restoration and maintenance of circulating blood volume where hypovolemia is demonstrated and colloid use is appropriate. When hypovolemia is long standing and hypoalbuminemia exists accompanied by adequate hydration or edema, 20-25% albumin solutions should be used.^1,2,3

Acute liver failure is a special situation in which both hypovolemia and hypoalbuminemia can be present. ALBUTEIN 5% can be used in such cases.^1

ALBUTEIN 5% may be of value in the treatment of shock or hypotension in renal dialysis patients.^1

1.2 Cardiopulmonary Bypass Procedures (Treatment Adjunct)

Preoperative dilution of blood using albumin and crystalloid can be used in cardiopulmonary bypass procedures. Albumin also may be used in the priming fluid.^4,5,6

1.3 Hypoalbuminemia

ALBUTEIN 5% may be indicated for subjects with hypoalbuminemia who are critically ill and/or actively bleeding. When albumin deficit is the result of excessive protein loss, the effect of ALBUTEIN 5% administration will be temporary unless the underlying disorder is reversed.^7,8,9 Septic patients and patients undergoing major surgery may lose more than half of their circulating plasma volume.^1,10 Treatment with ALBUTEIN 5% may be of value in such cases, especially when plasma colloid oncotic pressure is abnormally low.^1

In the first 24 hours after thermal injury, large volumes of crystalloids are infused to restore the depleted extracellular fluid volume. Beyond 24 hours, ALBUTEIN 5% can be used to maintain plasma colloid osmotic pressure.^2,11,12 Protein loss from the third space due to infection (acute peritonitis, pancreatitis, mediastinitis or extensive cellulitis) may require treatment with an infusion of albumin.^13,14

1.4 Plasma Exchange

ALBUTEIN 5% may be used as a replacement fluid during therapeutic Plasma Exchange treatments.^15

2 DOSAGE AND ADMINISTRATION

For Intravenous Use Only

2.1 Dosage

Adjust the concentration, dosage and infusion rate of the albumin preparation to the patient's individual requirements.

The dose required depends on the patient's body weight, severity of injury/illness and on continuing fluid and protein losses. Use adequacy of circulating blood volume, not plasma albumin levels, to determine the dose required.

Indication | Dose
Hypovolemia | Adults: Initial dose of 20 g. If hemodynamic stability is not achieved within 15 to 30 minutes, an additional dose may be given. Hemodilution may follow administration of ALBUTEIN 5%. Anemia resulting from hemorrhage should be corrected by administration of compatible red blood cells or compatible whole blood. For acute liver failure: initial dose of 12 to 25 g. An infusion rate of 1-2 mL per minute is usually indicated. For renal dialysis, the initial dose should not exceed 20 g and patients should be carefully observed for signs of fluid overload.
Cardiopulmonary bypass procedures | Adults: Initial dose of 25 g. Additional amounts may be administered as clinically indicated.
Hypoalbuminemia | Adults: 50 to 75 g For pre- and post-operative hypoproteinemia: 50 to 75 g. In burns, therapy usually starts with administration of large volumes of crystalloid solution to maintain plasma volume. After 24 hours: initial dose of 25 g and dose adjustment to maintain plasma protein concentration of 2.5 g per 100 mL or a serum protein concentration of 5.2 g per 100 mL. Third space protein loss due to infection: initial dose of 50 to 100 g. An infusion rate of 1-2 mL per minute is usually indicated in the absence of shock. Treatment should always be guided by hemodynamic response.
Plasma exchange | The dosage and infusion rate of ALBUTEIN 5% infused should be titrated to the volume of plasma removed during the procedure.

2.2 Administration

Intravenous use only

- ALBUTEIN 5% is a clear and slightly viscous solution. Visually inspect parenteral drug products for particulate matter and discoloration prior to administration, whenever solution and container permit. Do not use if the solution is turbid or if there is sediment in the bottle.
- Do not freeze.
- Warm product to room temperature before use if large volumes are administered.
- ALBUTEIN 5% contains no preservatives. Do not begin administration more than 4 hours after the container has been entered. Discard unused portion.
- Do not dilute with sterile water for injection [see Warnings and Precautions (5.6)].
- Adjust the infusion rate to the individual circumstances and the indication. In plasma exchange, adjust the infusion rate to the rate of plasma removal.

3 DOSAGE FORMS AND STRENGTHS

ALBUTEIN 5% is a solution containing 50 g per L of total protein of which at least 95% is human albumin.

4 CONTRAINDICATIONS

- Hypersensitivity to albumin preparations or to any of the excipients.
- Severe anemia or cardiac failure with normal or increased intravascular volume.

5 WARNINGS AND PRECAUTIONS

5.1 Hypersensitivity

Suspicion of allergic or anaphylactic reactions requires immediate discontinuation of the infusion and implementation of appropriate medical treatment.

5.2 Hypervolemia/Hemodilution

Hypervolemia may occur if the dosage and rate of infusion are not adjusted to the patient’s volume status. At the first clinical signs of fluid overload (headache, dyspnea, jugular venous distention, increased blood pressure), the infusion must be slowed or stopped immediately. Use albumin with caution in conditions where hypervolemia and its consequences or hemodilution could represent a special risk to the patient. Examples of such conditions are:

- Decompensated heart failure
- Hypertension
- Esophageal varices
- Pulmonary edema
- Hemorrhagic diathesis
- Severe anemia
- Renal and post-renal anuria

5.3 Electrolyte Imbalance

Monitor regularly the electrolyte status of the patient and take appropriate steps to restore or maintain the electrolyte balance when albumin is administered.

5.4 Coagulation Abnormalities

Regular monitoring of coagulation and hematology parameters is necessary if comparatively large volumes are to be replaced. Care must be taken to ensure adequate substitution of other blood constituents (coagulation factors, electrolytes, platelets, and erythrocytes).

5.5 Laboratory Monitoring

Monitor regularly hemodynamic parameters during administration of ALBUTEIN 5%; this may include:

- Arterial blood pressure and pulse rate
- Central venous pressure
- Pulmonary artery occlusion pressure
- Urine output
- Electrolytes
- Hematocrit/hemoglobin

5.6 Application Precautions

ALBUTEIN 5% must not be diluted with sterile water for injection as this may cause hemolysis in recipients [see Dosage and Administration (2.2)].

5.7 Transmissible Infectious Agents

Albumin is a derivative of human blood. Based on effective donor screening and product manufacturing processes, it carries an extremely remote risk for transmission of viral diseases and variant Creutzfeldt-Jakob disease (vCJD). There is a theoretical risk for transmission of Creutzfeldt-Jakob disease (CJD), but if that risk actually exists, the risk of transmission would also be considered extremely remote. No cases of transmission of viral diseases, CJD or vCJD have ever been identified for ALBUTEIN 5%.

6 ADVERSE REACTIONS

The most serious adverse reactions are anaphylactic shock, heart failure and pulmonary edema. The most common adverse reactions are anaphylactoid type reactions.

Adverse reactions to ALBUTEIN 5% normally resolve when the infusion rate is slowed or the infusion is stopped. In case of severe reactions, the infusion is stopped and appropriate treatment initiated.

6.1 Clinical Trials Experience

No clinical studies were done using ALBUTEIN 5%.

6.2 Post-Marketing Experience

Because adverse reactions are reported voluntarily post-approval from a population of uncertain size, it is not always possible to reliably estimate their frequency or to establish a causal relationship to product exposure. The following adverse reactions have been identified during post approval use of human albumin, including ALBUTEIN (all strengths) in decreasing order of significance:

- Anaphylactic shock
- Heart failure
- Pulmonary edema
- Hypotension
- Tachycardia
- Vomiting
- Urticaria
- Rash
- Headache
- Chills
- Fever
- Flushing
- Nausea

7 DRUG INTERACTIONS

ALBUTEIN 5% must not be mixed with other medicinal products.

8 USE IN SPECIFIC POPULATIONS

8.1 Pregnancy

Risk Summary
There is no data with ALBUTEIN 5% use in pregnant women to inform a drug-associated risk. Animal reproduction studies have not been conducted with ALBUTEIN 5%. It is not known whether ALBUTEIN 5% can cause fetal harm when administered to a pregnant woman or can affect reproduction capacity. ALBUTEIN 5% should be given to a pregnant woman only if clearly needed. In the U.S. general population, the estimated background risk of major birth defect and miscarriage in clinically recognized pregnancies is 2-4% and 15-20%, respectively.

8.2 Lactation

Risk Summary
There is no information regarding the presence of ALBUTEIN 5% in human milk, the effect on the breastfed infant, or the effects on milk production. The developmental and health benefits of breastfeeding should be considered along with the mother’s clinical need for ALBUTEIN 5% and any potential adverse effects on the breastfed infant from ALBUTEIN 5%.

8.4 Pediatric Use

No human or animal data. Use only if clearly needed.

8.5 Geriatric Use

No human or animal data. Use only if clearly needed.

11 DESCRIPTION

ALBUTEIN 5% is a sterile, aqueous solution for single dose intravenous administration containing 5% human albumin (weight/volume). ALBUTEIN 5% is prepared by a cold alcohol fractionation method from pooled human plasma obtained from venous blood. The product is stabilized with 0.08 millimole sodium caprylate and 0.08 millimole sodium acetyltryptophanate per gram of protein.

ALBUTEIN 5% is osmotically and isotonically equivalent to an equal volume of normal human plasma.

A liter of ALBUTEIN 5% solution contains 130-160 milliequivalents of sodium ion. The aluminum content of the solution is not more than 200 micrograms per liter during the shelf life of the product. The product contains no preservatives.

ALBUTEIN 5% is manufactured from Source Plasma collected from FDA approved plasmapheresis centers in the United States. ALBUTEIN 5% is heated at 60 °C for ten hours, a process that has the capacity to inactivate viruses.

12 CLINICAL PHARMACOLOGY

12.1 Mechanism of Action

Human Albumin accounts for more than half of the total protein in the plasma and represents about 10% of protein synthesis activity by the liver.

Human Albumin 5% is almost isooncotic to normal plasma.

The primary physiological function of albumin results from its contribution to plasma colloid oncotic pressure and transport function. Albumin stabilizes circulating blood volume and is a carrier of hormones, enzymes, medicinal products and toxins. Other physiological functions include antioxidant properties, free radical scavenging and capillary membrane integrity.

12.3 Pharmacokinetics

Albumin is distributed throughout the extracellular space and more than 60% of the body albumin pool is located in the extravascular fluid compartment. Albumin has a circulating life span of 15-20 days, with a turnover of approximately 15 g per day.

The balance between synthesis and breakdown is normally achieved by feedback regulation.

Elimination is predominantly intracellular and due to lysosome proteases.

In healthy subjects, less than 10% of infused albumin leaves the intravascular compartment during the first 2 hours following infusion. There is considerable individual variation in the effect of albumin on plasma volume. In some patients, plasma volume can remain elevated for several hours. In critically ill patients, however, albumin can leak out of the vascular space in substantial amounts at an unpredictable rate.

15 REFERENCES

1. Tullis JL. Albumin: 1. Background and Use. 2. Guidelines for Clinical Use. JAMA. 1977; 237:355-360, 460-463.
2. Vermeulen LC, et al. A Paradigm for Consensus. Arch Intern Med. 1995;155:373-379.
3. SAFE Study investigators. A comparison of albumin and saline for fluid resuscitation in the intensive care unit. N Engl J Med. 2004;350:2247-2256.
4. Sedrakyan A, Gondek K, Paltiel D, et al. Volume expansion with albumin decreases mortality after coronary artery bypass graft surgery. Chest. 2003;123:1853-1857.
5. Russell JA, Navickis RJ, Wilkes MM. Albumin versus crystalloid for pump priming in cardiac surgery: meta-analysis of controlled trials. J Cardiothorac Vasc Anesth. 2004;18:429-37.
6. American Thoracic Society. Evidence-based colloid use in the critically ill: American Thoracic Society consensus statement. Am J Respir Crit Care Med. 2004;170:1247-59.
7. Mendez CM, McClain CJ, Marsano LS. Albumin Therapy in Clinical Practice. Nutrition in Clinical Practice. 2005;20:314-320.
8. Haynes GR, Navickis RJ, Wilkes MM. Albumin administration-what is the evidence of clinical benefit? A systematic review of randomized controlled trials. Eur J Anaesthesiol. 2003 Oct;20(10):771-93.
9. Vincent JL, Navickis RJ, Wilkes MM. Morbidity in hospitalized patients receiving human albumin: a meta-analysis of randomized, controlled trials. Crit Care Med. 2004;32:2029-38.
10. Skillman JJ, Tanenbaum BJ. Current Topics in Surgical Research. Vol. 2. New York: Academic Press. 1970;523.
11. Muir IA, Barclay TL. Burns and their treatment. Chicago: Year Book Medical Publishers. 1974.
12. Pruitt BA Jr, Goodwin CW Jr. Current treatment of the extensively burned patient. Surg Annu. 1983;15:331-64.
13. Clowes GHA Jr, Vucinic M, Weidner MG. Circulatory and metabolic alterations associated with survival or death in peritonitis: clinical analysis of 25 cases. Ann Surg. 1966;166:866-85.
14. Sort P, Navasa M, Arroyo V, et al. Effect of intravenous albumin on renal impairment and mortality in patients with cirrhosis and spontaneous bacterial peritonitis. N Engl J Med. 1999;341:403-409.
15. Szczepiorkowski ZM, Bandarenko N, Kim HC, et al. Guidelines on the use of therapeutic apheresis in clinical practice-evidence-based approach from the Apheresis applications committee of the American Society for Apheresis. J Clin Apheresis. 2007;22:106-175.

16 HOW SUPPLIED/STORAGE AND HANDLING

ALBUTEIN 5% is supplied in single-use, individually laser etched vials.

The following vial sizes of ALBUTEIN 5% are available:

NDC Number Fill Size Grams Protein
68516-5214-5 50 mL 2.5 g
68516-5214-1 250 mL 12.5 g
68516-5214-2 500 mL 25 g

Each vial size label incorporates integrated hangers. Each label has a peel-off strip showing the product name and lot number.

ALBUTEIN 5% is stable for three years provided the storage temperature does not exceed 30 °C. Protect from freezing.

17 PATIENT COUNSELING INFORMATION

This product is usually given in a hospital setting.

Inform patients being treated with ALBUTEIN 5% about the risks and benefits of its use [see Adverse Reactions (6)].

Inform patients to immediately report the following signs and symptoms to their physician:

- Allergic or anaphylactic type reactions [see Warnings and Precautions (5.1)].
- Cardiovascular overload (e.g., headache, dyspnea and jugular venous distention) [see Warnings and Precautions (5.2)].
- Increased blood pressure, raised venous pressure and pulmonary edema [see Warnings and Precautions (5.2)].

Inform patients that ALBUTEIN 5% is a derivative of human plasma and may contain infectious agents that cause disease (e.g., viruses, and theoretically, the CJD agent). Inform patients that the risk that ALBUTEIN 5% may transmit an infectious agent has been reduced by screening plasma donors for prior exposure to certain viruses, by testing the donated plasma for certain viral agents and by the introduction of steps with capacity for the inactivation and/or removal of certain viruses during the manufacturing process [see Warnings and Precautions (5.7)].

Manufactured by:
Grifols Biologicals LLC
5555 Valley Boulevard
Los Angeles, CA 90032, U.S.A.
U. S. License No. 1694

3063731

Principal Display Panel – 50 mL Vial Label

NDC 68516-5214-6 2.5 g / 50 mL
Albumin (Human) U.S.P
Albutein® 5%
Solution
5%
Rx Only
Precautions: Do not allow to freeze. Single dose container for intravenous
administration. Discard any unused contents and administration devices
after use.
Instructions: The patient and physician should discuss the risks and benefits
of this product. For information on dosage and directions for administration,
see accompanying pamphlet.
Contents: Each 50 mL contains 2.5 grams Albumin (Human) in aqueous
diluent. Osmotically and isotonically equivalent to an equal volume of
normal human plasma. Sodium range 130-160 milliequivalents per liter.
Contains no preservatives. Heat-treated at 60 °C for 10 hours.
Store at temperatures not exceeding 30 °C.
DO NOT USE IF TURBID. DO NOT BEGIN ADMINISTRATION MORE THAN
4 HOURS AFTER THE CONTAINER HAS BEEN ENTERED.
Grifols Biologicals LLC
Los Angeles, CA 90032, USA
U.S. License No. 1694
Lot No.:
Expires:
3064240

Principal Display Panel – 50 mL Carton Label
NDC 68516-5214-5 2.5 g / 50 mL
Albumin (Human) U.S.P.
Albutein® 5%
Solution
5%
Store at temperatures
not exceeding 30° C.
Rx only
Precautions:
Do not allow to freeze.
Single dose container for intravenous
administration.
Discard any unused contents and
administration devices after use.
Instructions:
The patient and physician should discuss
the risks and benefits of this product. For
information on dosage and directions for
administration, see enclosed pamphlet.
DO NOT USE IF TURBID.
DO NOT BEGIN ADMINISTRATION MORE
THAN 4 HOURS AFTER THE CONTAINER
HAS BEEN ENTERED.
GRIFOLS
Contents:
One 50 mL vial Albumin (Human) U.S.P.
Albutein®. Each 50 mL contains 2.5 grams
Albumin (Human) in aqueous diluent.
Osmotically and isotonically equivalent to
an equal volume of normal human plasma.
Sodium range 130-160 milliequivalents
per liter.
Stabilized with 0.08 millimole sodium
caprylate and 0.08 millimole sodium
acetyltryptophanate per gram of albumin.
Contains no preservatives.
Heat-treated at 60 °C for 10 hours
Grifols Biologicals LLC
Los Angeles, CA 90032, USA
U.S. License No. 1694
GTIN 00368516521458
Lot XXXXXXXXXX
EXP DDMMMYYYY
SN XXXXXXXXXXXXXXXX
3064248

Principal Display Panel – 250 mL Vial Label

NDC 68516-5214-3 12.5 g / 250 mL
Albumin (Human)
U.S.P.
Albutein® 5%
Solution
5%
GRIFOLS Rx only
Precautions: Do not allow to freeze. Single dose container for
intravenous administration. Discard any unused contents and
administration devices after use.
Instructions: The patient and physician should discuss the risks and
benefits of this product. For information on dosage and directions for
administration, see accompanying pamphlet.
Contents: Each 250 mL contains 12.5 grams Albumin (Human) in
aqueous diluent. Osmotically and isotonically equivalent to an equal
volume of normal human plasma.
Sodium range 130-160 milliequivalents per liter.
Contains no preservatives. Heat-treated at 60 °C for 10 hours.
Store at temperatures not exceeding 30 °C.
DO NOT USE IF TURBID. DO NOT BEGIN ADMINISTRATION MORE
THAN 4 HOURS AFTER THE CONTAINER HAS BEEN ENTERED.
Grifols Biologicals LLC
Los Angeles, CA 90032, USA
U.S. License No. 1694
Lot No.:
Expires:
3063730

Principal Display Panel – 250 mL Carton Label

NDC 68516-5214-1 12.5 g/ 250 mL
Albumin (Human)
U.S.P.
Albutein® 5%
Solution
5%
Store at temperatures
not exceeding 30° C
Grifols
Rx only
Precautions:
Do not allow to freeze.
Single dose container for intravenous
administration.
Discard any unused contents and
administration devices after use.
Instructions:
The patient and physician should discuss
the risks and benefits of this product. For
information on dosage and directions for
administration, see enclosed pamphlet.
DO NOT USE IF TURBID.
DO NOT BEGIN ADMINISTRATION MORE THAN
4 HOURS AFTER THE CONTAINER HAS BEEN
ENTERED.
GRIFOLS
Contents:
One 250 mL vial Albumin (Human) U.S.P.
Albutein®. Each 250 mL contains 12.5 grams
Albumin (Human) in aqueous diluent.
Osmotically and isotonically equivalent to an
equal volume of normal human plasma.
Sodium range 130_160 milliequivalents per liter.
Stabilized with 0.08 millimole sodium caprylate
and 0.08 millimole sodium acetyltryptophanate
per gram of albumin.
Contains no preservatives.
Heat-treated at 60 °C for 10 hours
Grifols Biologicals LLC
Los Angeles, CA 90032, USA
U.S. License No. 1694
GTIN 00368516521410
LOT XXXXXXXXXX
EXP DDMMMYYYY
SN XXXXXXXXXXXXXXXX
3063729

Principal Display Panel – 500 mL Vial Label

NDC 68516-5214-4 25 g / 500 mL
Albumin (Human)
U.S.P.
Albutein® 5%
Solution
5%
GRIFOLS Rx only
Precautions: Do not allow to freeze. Single dose container for
intravenous administration. Discard any unused contents and
administration devices after use.
Instructions: The patient and physician should discuss the risks
and benefits of this product. For information on dosage and
directions for administration, see accompanying pamphlet.
Contents: Each 500 mL contains 25 grams Albumin (Human) in
aqueous diluent. Osmotically and isotonically equivalent to an equal
volume of normal human plasma.
Sodium range 130-160 milliequivalents per liter.
Contains no preservatives.
Heat-treated at 60 °C for 10 hours.
Store at temperatures not exceeding 30 °C.
DO NOT USE IF TURBID. DO NOT BEGIN ADMINISTRATION MORE
THAN 4 HOURS AFTER THE CONTAINER HAS BEEN ENTERED.
Grifols Biologicals LLC
Los Angeles, CA 90032, USA
U.S. License No. 1694
Lot No.:
Expires:
3063727

Principal Display Panel – 500 mL Carton Label

NDC 68516-5214-2 25 g / 500 mL
Albumin (Human)
U.S.P.
Albutein® 5%
Solution
5%
Store at temperatures
not exceeding 30° C.
Rx only
Precautions:
Do not allow to freeze.
Single dose container for intravenous
administration.
Discard any unused contents and administration
devices after use.
Instructions:
The patient and physician should discuss
the risks and benefits of this product. For
information on dosage and directions for
administration, see enclosed pamphlet.
DO NOT USE IF TURBID.
DO NOT BEGIN ADMINISTRATION MORE THAN
4 HOURS AFTER THE CONTAINER HAS BEEN
ENTERED.
GRIFOLS
Contents:
One 500 mL vial Albumin (Human) U.S.P.
Albutein®. Each 500 mL contains 25 grams
Albumin (Human) in aqueous diluent.
Osmotically and isotonically equivalent to an
equal volume of normal human plasma.
Sodium range 130_160 milliequivalents per liter.
Stabilized with 0.08 millimole sodium caprylate
and 0.08 millimole sodium acetyltryptophanate
per gram of albumin.
Contains no preservatives.
Heat-treated at 60 °C for 10 hours
Grifols Biologicals LLC
Los Angeles, CA 90032, USA
U.S. License No. 1694
GTIN 00368516521427
LOT XXXXXXXXXX
EXP DDMMMYYYY
SN XXXXXXXXXXXXXXXX
3063726